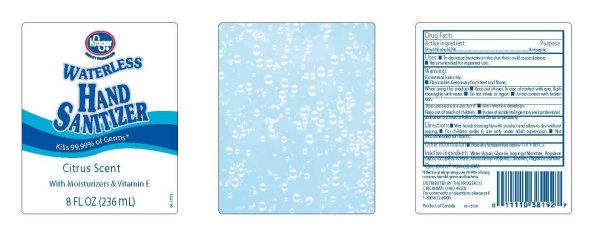 DRUG LABEL: Kroger Waterless Hand Sanitizer Citrus Scent With Moisturizers And Vitamin E
NDC: 59450-200 | Form: GEL
Manufacturer: The Kroger Co.
Category: otc | Type: HUMAN OTC DRUG LABEL
Date: 20091214

ACTIVE INGREDIENTS: ALCOHOL 62 mL/100 mL
INACTIVE INGREDIENTS: WATER; GLYCERIN; CARBOMER HOMOPOLYMER TYPE C; PROPYLENE GLYCOL; ISOPROPYL MYRISTATE; ALPHA-TOCOPHEROL ACETATE

Kroger Waterless Hand Sanitizer Citrus Scent With Moisturizers & Vitamin E

Active Ingredient Purpose

Ethyl Alchohol 62 Percent Antiseptic

Uses

To decrease bacteria on the skin that could cause disease.

Recommended for repeated use.

Warnings

For external use only.

Flammable. Keep away from heat and flame.

When using this product

Keep out of eyes. In case of contact with eyes, flush thoroughly with water.
Do not inhale or ingest.
Avoid contact with broken skin.

Stop use and ask a doctor if skin irritation develops.

Keep out of reach of children.

In case of accidental ingestion, seek professional assistance or contact a Poison Control Center immediately.

Directions

Wet hand thoroughly with product and allow to dry without wiping.

For children under 6, use only under adult supervision.

Not recommended for infants.

Other information:

Store at a temperature below 110 degrees F (43 degrees C)

Questions? 1 800 632 6900

INACTIVE INGREDIENT

Inactive ingredients: Water aqua, Isopropyl Myristate, Propylene Glycol,

Tocopheryl Acetate, Aminomethyl Propanol, Carbomer, Fragrance Parfum

DESCRIPTION

Effective at eliminating over 99.99 percent of many common harmful germs and bacteria.

Distributed by:
THE KROGER CO.
CINCINNATI, OHIO 45202
For comments or questions please call
1 800 632 6900
Product of Canada

PACKAGE LABEL

Kroger

Waterless Hand Sanitizer

Kills 99.99 percent of germs

Citrus Scent

With Moisturizers and Vitamin E

8 Fl OZ 236 ml